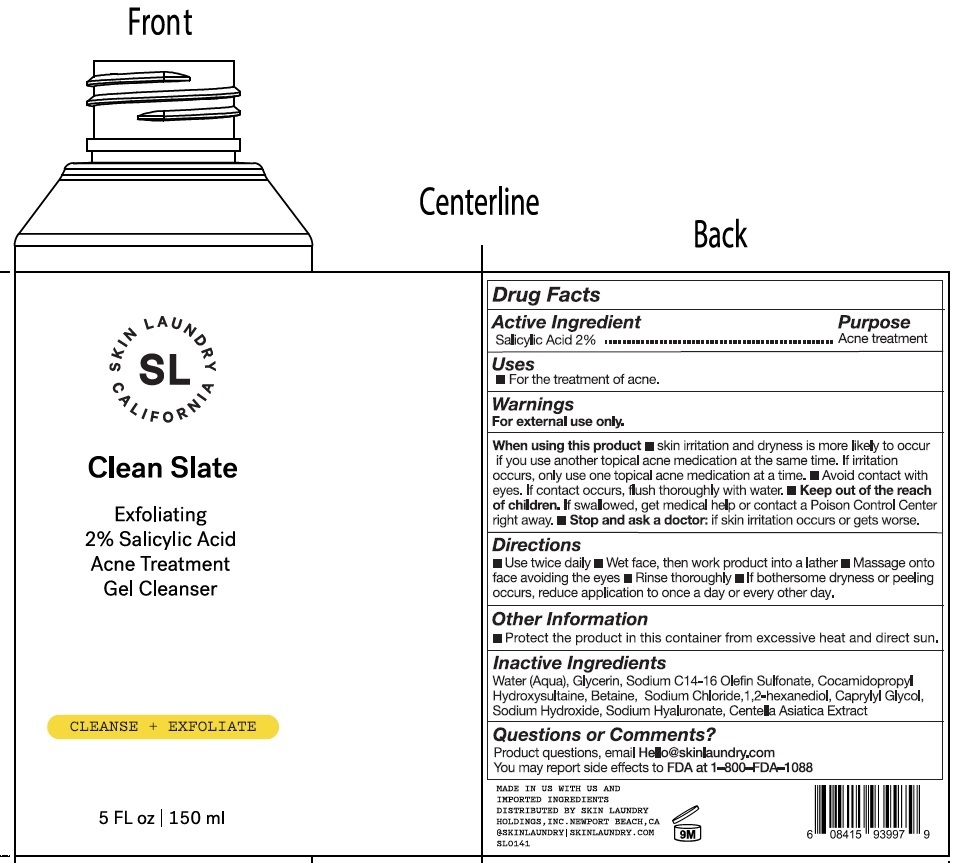 DRUG LABEL: Skin Laundry. Clean Slate Exfoliating 2 Salicylic Acid Treatment Gel Cleanser Cleanse Exfoliate
NDC: 83727-294 | Form: GEL
Manufacturer: Skin Laundry Holdings, Inc.
Category: otc | Type: HUMAN OTC DRUG LABEL
Date: 20231006

ACTIVE INGREDIENTS: SALICYLIC ACID 20 mg/1 mL
INACTIVE INGREDIENTS: WATER; GLYCERIN; COCAMIDOPROPYL HYDROXYSULTAINE; BETAINE; SODIUM CHLORIDE; 1,2-HEXANEDIOL; CAPRYLYL GLYCOL; SODIUM HYDROXIDE; HYALURONATE SODIUM; CENTELLA ASIATICA TRITERPENOIDS; SODIUM C14-16 OLEFIN SULFONATE

Skin Laundry. Clean Slate Exfoliating 2% Salicylic Acid Treatment Gel Cleanser Cleanse + Exfoliate

Active ingredient

Salicylic Acid 2%

Purpose

Acne treatment

Uses

● For the treatment of acne.

Warnings

For external use only.

When using this product

- skin irritation and dryness is more likely to occur if you use another topical acne medication at the same time. If irritation occurs, only use one topical acne medication at a time.
- Avoid contact with eyes. If contact occurs, flush thoroughly with water.

Keep out of the reach of children.

- If swallowed, get medical help or contact a Poison Control Center right away.

Stop and ask a doctor:

if skin irritation occurs or gets worse

Directions

- Use twice daily
- Wet face, then work product into a lather
- Massage onto face avoiding the eyes
- Rinse thoroughly
- If bothersome dryness or peeling occurs, reduce application to once a day or every other day.

Other Information

- Protect the product in this container from excessive heat and direct sun.

Inactive Ingredients

Water (Aqua), Glycerin, Sodium C14-16 Olefin Sulfonate, Cocamidopropyl Hydroxysultaine, Betaine, Sodium Chloride, 1,2-hexanediol, Caprylyl Glycol, Sodium Hydroxide, Sodium Hyaluronate, Centelia Asiatica Extract

Questions or Comments?

Product questions, email Hello@skinlaundry,com

You may report side effects to FDA at 1-800-FDA-1088